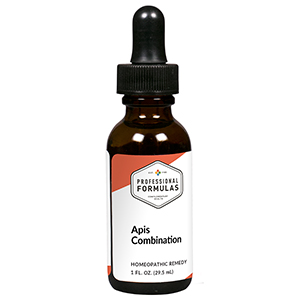 DRUG LABEL: Apis Combination
NDC: 63083-9206 | Form: LIQUID
Manufacturer: Professional Complementary Health Formulas
Category: homeopathic | Type: HUMAN OTC DRUG LABEL
Date: 20190815

ACTIVE INGREDIENTS: APIS MELLIFERA 2 [hp_X]/29.5 mL; ANTIMONY POTASSIUM TARTRATE 6 [hp_X]/29.5 mL; APIS MELLIFERA VENOM 6 [hp_X]/29.5 mL; DRIMIA MARITIMA BULB 6 [hp_X]/29.5 mL; PROPIONIBACTERIUM ACNES 12 [hp_X]/29.5 mL
INACTIVE INGREDIENTS: ALCOHOL; WATER

R206

ACTIVE INGREDIENTS

Apis mellifica 2X, 10X, 200X, 1000X
Antimonium tartaricum 6X, 10X, 30X, 200X
Apis venenum purum 6X, 30X
Scilla maritima 6X, 10X, 30X
Acne nosode 12X

QUESTIONS

Professional Formulas

PO Box 2034 Lake Oswego, OR 97035

INDICATIONS

For the temporary relief of dry, irritated, red, or itchy skin, minor swelling, or acne.*

PURPOSE

*Claims based on traditional homeopathic practice, not accepted medical evidence. Not FDA evaluated.

WARNINGS

In case of overdose, get medical help or contact a poison control center right away.

Keep out of the reach of children.

PREGNANCY OR BREAST FEEDING

If pregnant or breastfeeding, ask a healthcare professional before use.

DIRECTIONS

Place drops under tongue 30 minutes before/after meals. Adults and children 12 years and over: Take 10 drops up to 3 times per day. Consult a physician for use in children under 12 years of age.

OTHER INFORMATION

Tamper resistant. If seal is broken, do not use. After opening, close container tightly and store at room temperature away from heat.

INACTIVE INGREDIENTS

40% ethanol, purified water.

LABEL

Est 1985

Professional Formulas

Complementary Health

Apis Combination

Homeopathic Remedy

1 FL. OZ. (29.5 mL)